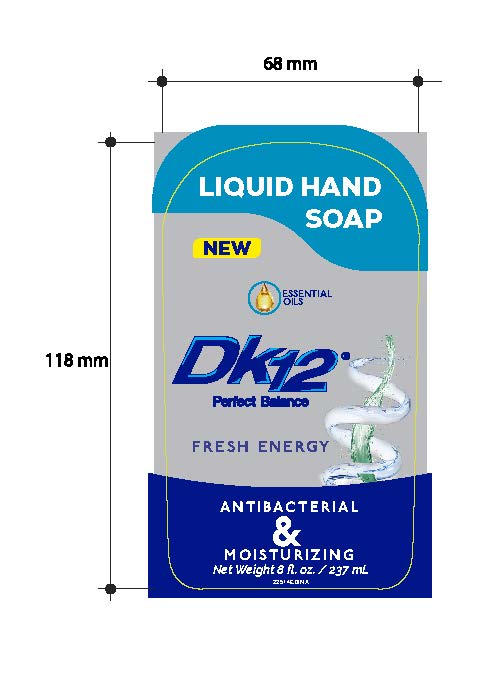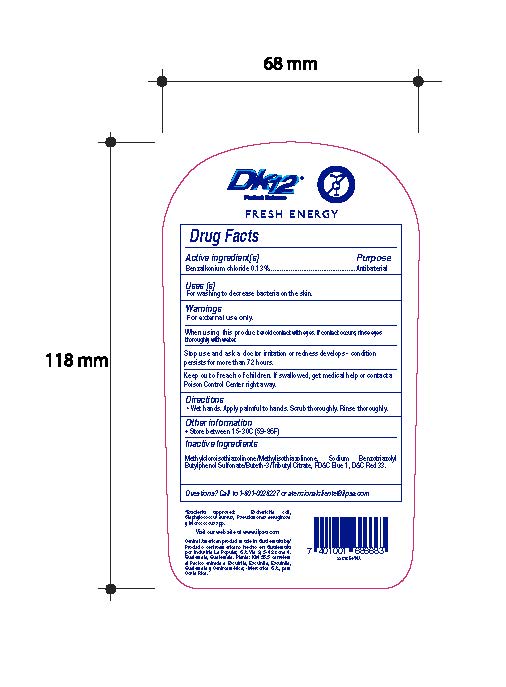 DRUG LABEL: DK12 Liquid Hand Fresh Energy
NDC: 62476-007 | Form: LIQUID
Manufacturer: Industria La Popular, S.A.
Category: otc | Type: HUMAN OTC DRUG LABEL
Date: 20241202

ACTIVE INGREDIENTS: BENZALKONIUM CHLORIDE 0.65 g/500 mL
INACTIVE INGREDIENTS: SODIUM BENZOTRIAZOLYL BUTYLPHENOL SULFONATE; BUTETH-3; METHYLCHLOROISOTHIAZOLINONE; TRIBUTYL CITRATE; FD&C BLUE NO. 1; D&C RED NO. 33; METHYLISOTHIAZOLINONE

DK12 Liquid Hand Soap Fresh Energy

Active Ingredient

Benzalkonium Chloride 0.13%

Purpose

Antibacterial

Uses

For washing to decrease bacteria on the skin

Warnings

For External Use only.

When using this product

avoid contact with eyes. If contact occurs, rinse eyes thoroughly with water.

Stop use and ask a doctor

irritation or redness develops - condition persists for more than 72 hours.

Keep out of reach of children.

If swallowed, get medical help or contact a Poison Control Center right away

Directions

Wet hands. Apply palmful to hands. Scrub thoroughly. Rinse thoroughly.

Other Information

Store between 15-30C (59-86F)

Inactive Ingredients

Methylcloroisothiazolinone/Methylisothiazolinone, Sodium Benzotriazolyl Butylphenol Sulfonate/Buteth-3/Tributyl Citrate, FD&C Blue 1, D&C Red 33.